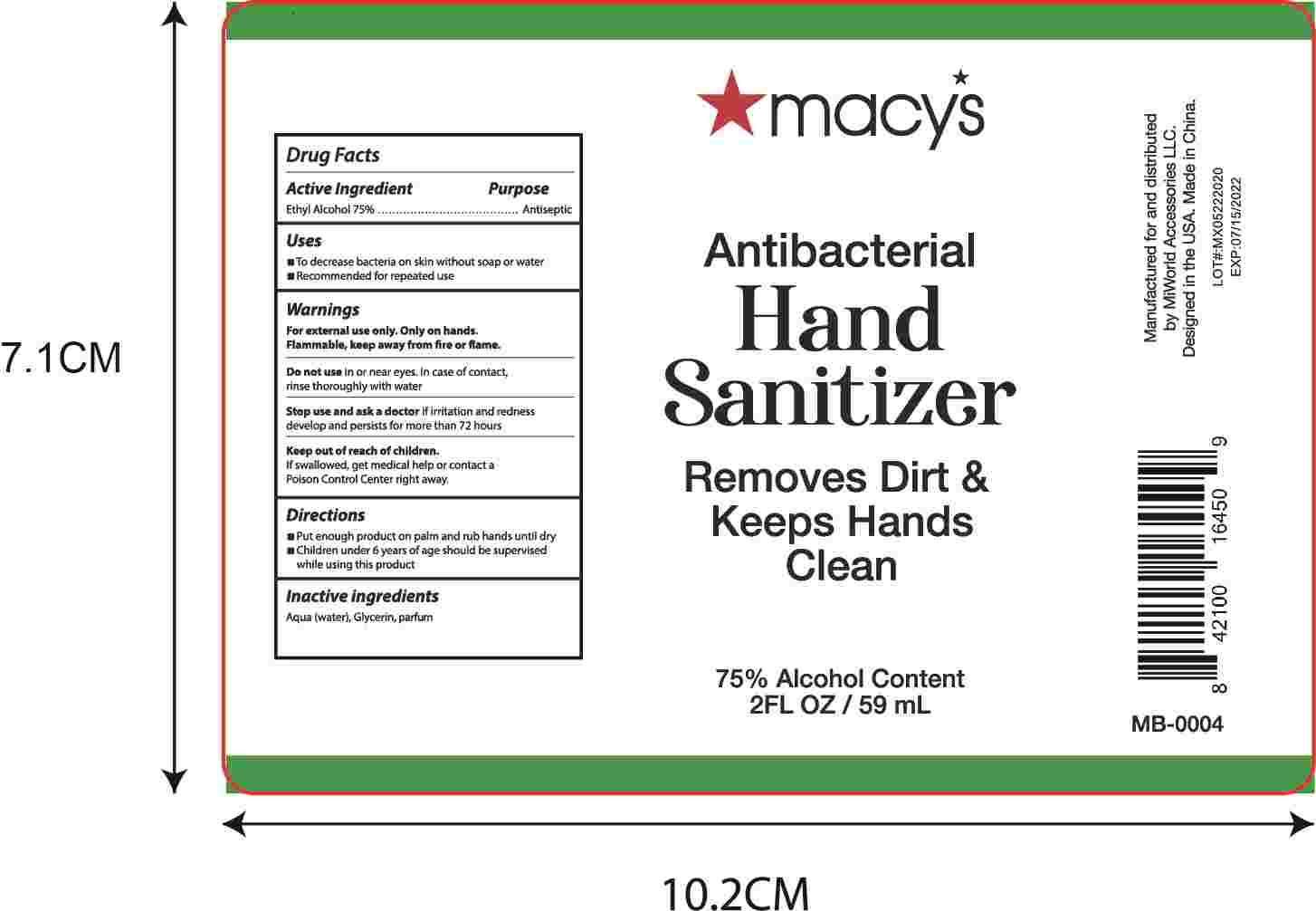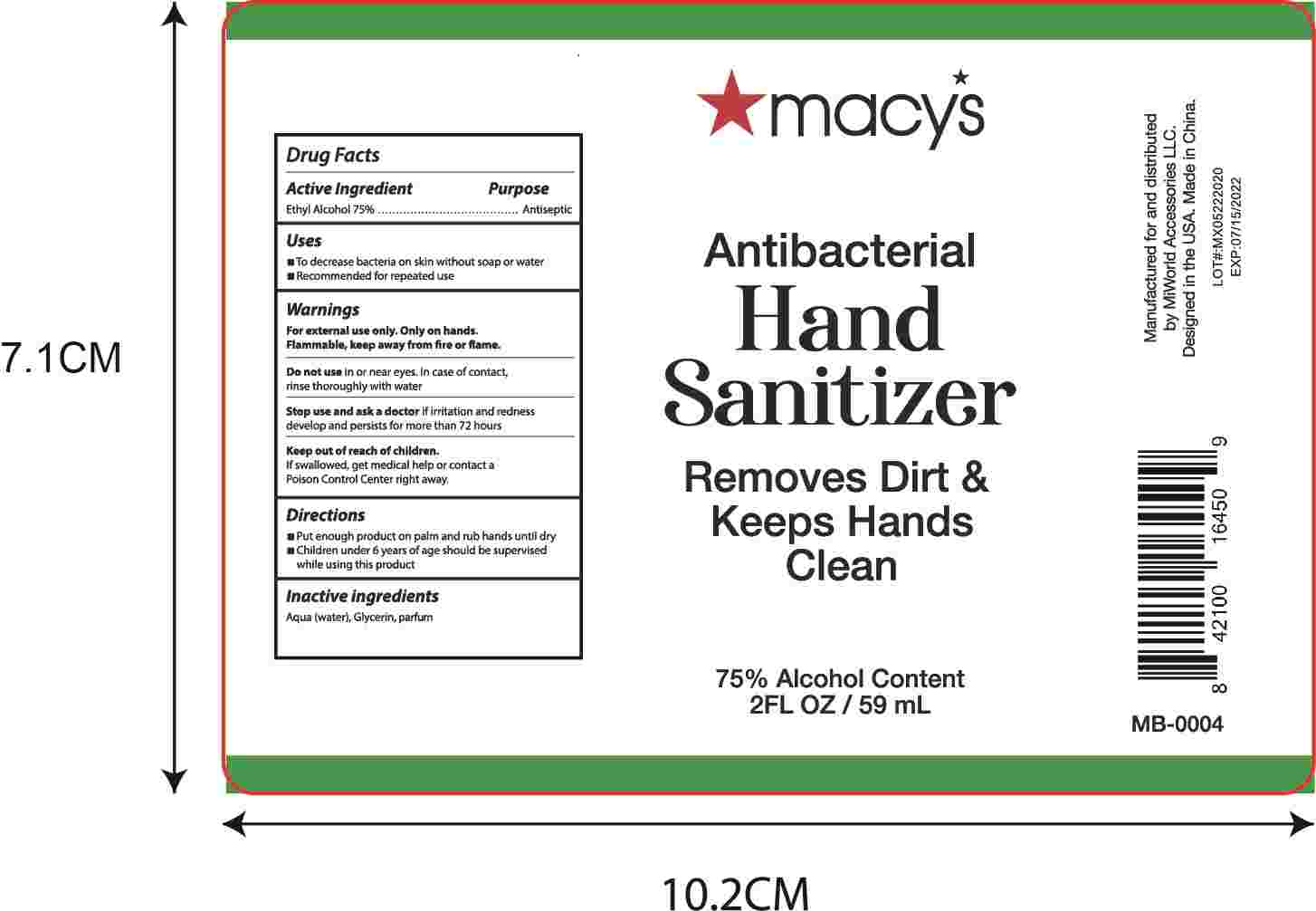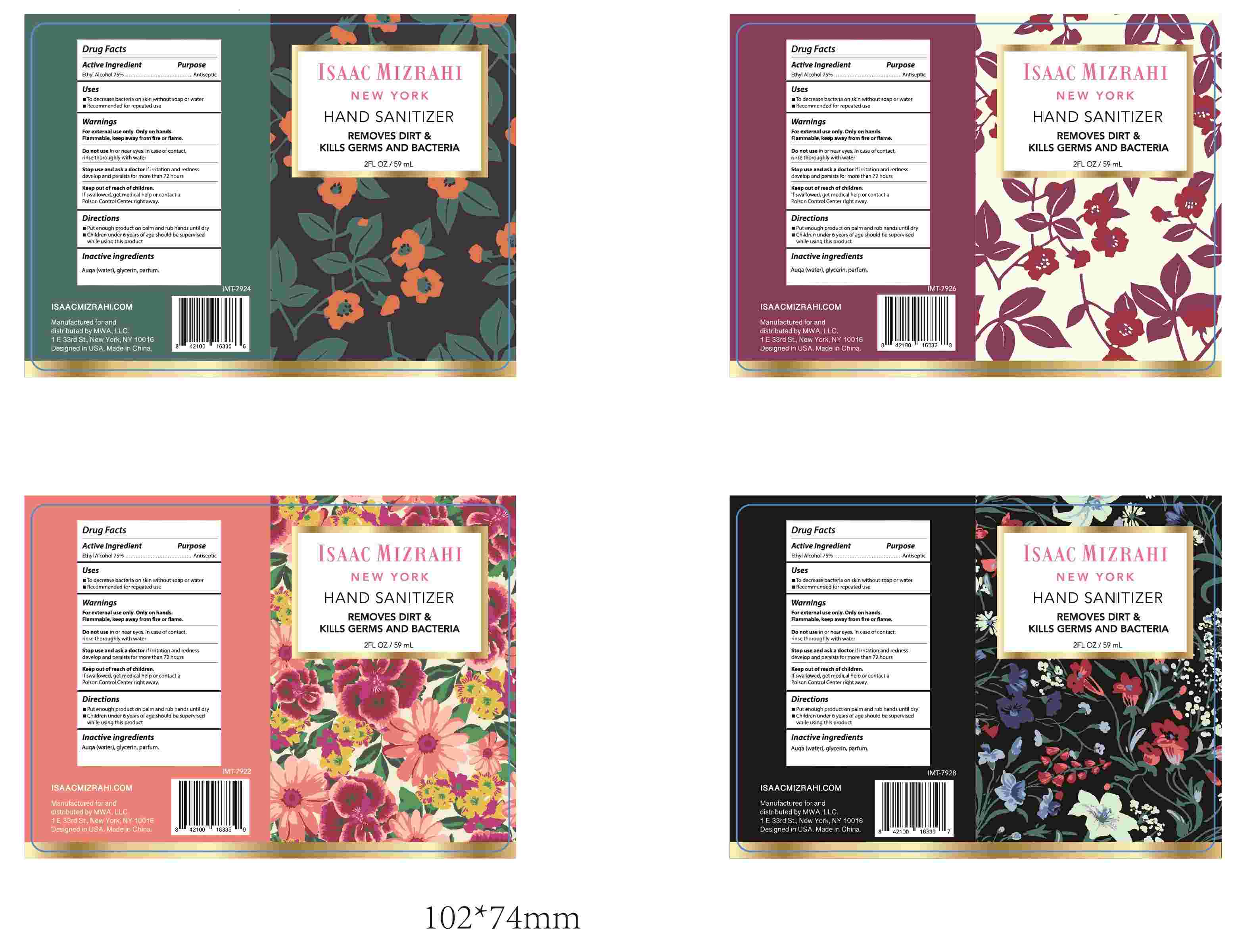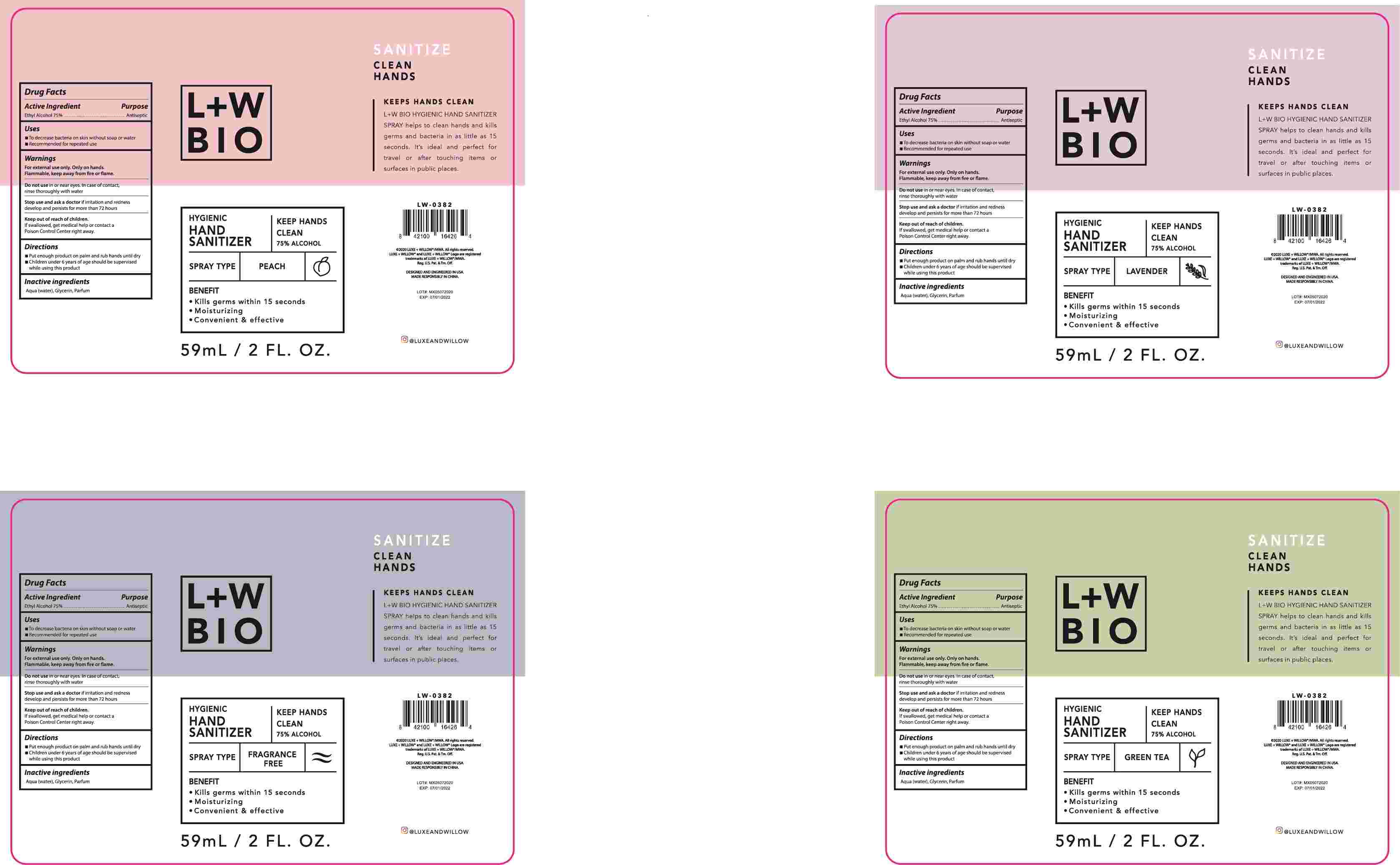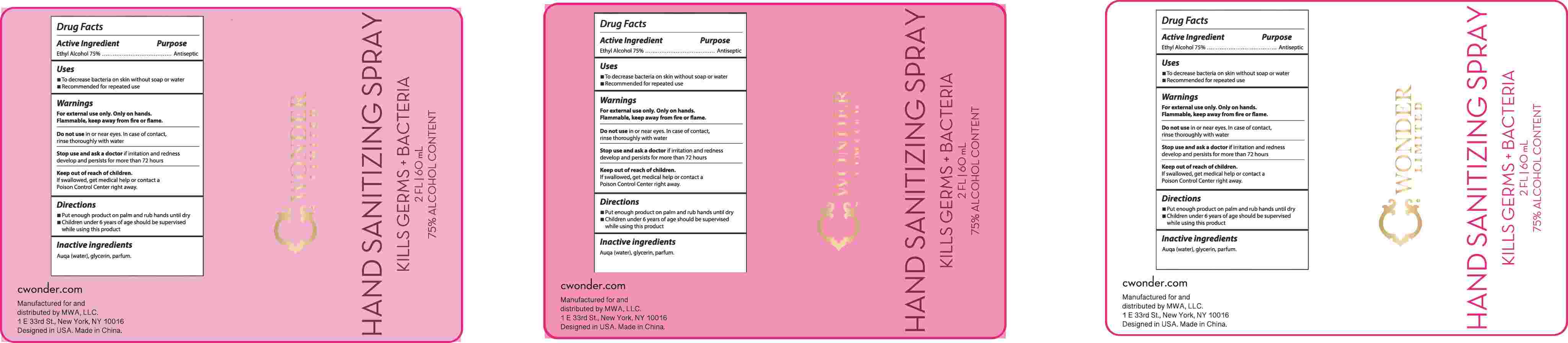 DRUG LABEL: Hand Sanitizer
NDC: 78565-002 | Form: SPRAY
Manufacturer: Meixin Beauty & Health Care Products Co., Ltd.
Category: otc | Type: HUMAN OTC DRUG LABEL
Date: 20200702

ACTIVE INGREDIENTS: ALCOHOL 75 mL/100 mL
INACTIVE INGREDIENTS: METHYL BENZOATE; GLYCERIN; WATER

Hand Sanitizer Spray

Active Ingredient(s)

Ethyl Alcohol 75% v/v

Purpose

Antimicrobial

Warnings

For external use only. Only on hands
Flammable, keep away from fire or flam

Do not use in or near eyes In case of contact
rinse thoroughly with water

WHEN USING

/

Stop use and ask a doctor if irritation and redness
develop and persists for more than 72 hours

Keep out of reach of children
If swallowed, get medical help or contact a
Poison Control Center right away

Directions

Put enough product on palm and rub hands until drya
Children under 6 years of age should be supervised while using this

product

Other information

/

Inactive ingredients

Auqa(water), glycerin, parfum

INDICATIONS AND USAGE

To decrease bacteria on skin without soap or water
Recommended for repeated use